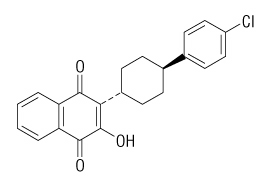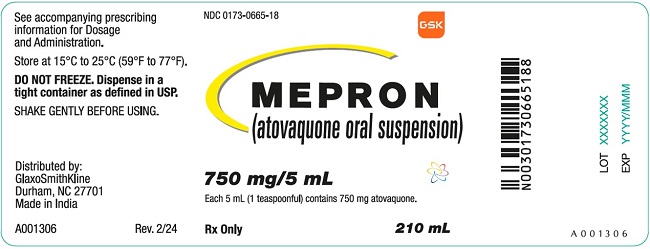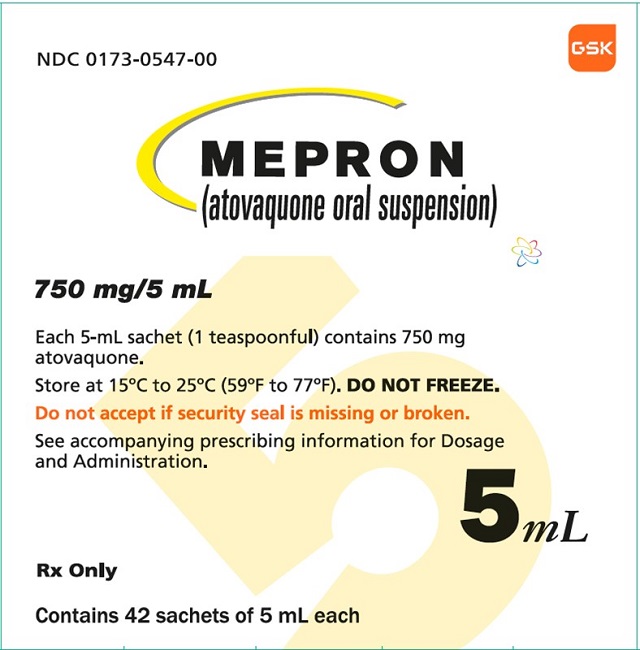 DRUG LABEL: MEPRON
NDC: 0173-0665 | Form: SUSPENSION
Manufacturer: GlaxoSmithKline LLC
Category: prescription | Type: HUMAN PRESCRIPTION DRUG LABEL
Date: 20230720

ACTIVE INGREDIENTS: ATOVAQUONE 750 mg/5 mL
INACTIVE INGREDIENTS: BENZYL ALCOHOL; POLOXAMER 188; WATER; SACCHARIN SODIUM; XANTHAN GUM

HIGHLIGHTS OF PRESCRIBING INFORMATION

These highlights do not include all the information needed to use MEPRON oral suspension safely and effectively. See full prescribing information for MEPRON oral suspension.
MEPRON (atovaquone oral suspension)
Initial U.S. Approval: 1992

1 INDICATIONS AND USAGE

MEPRON oral suspension is a quinone antimicrobial drug indicated for:

- Prevention of Pneumocystis jirovecii pneumonia (PCP) in adults and adolescents aged 13 years and older who cannot tolerate trimethoprim-sulfamethoxazole (TMP-SMX). (1.1)
- Treatment of mild-to-moderate PCP in adults and adolescents aged 13 years and older who cannot tolerate TMP-SMX. (1.2)

Limitations of Use (1.3):

- Treatment of severe PCP (alveolar arterial oxygen diffusion gradient [(A-a)DO2] >45 mm Hg) with MEPRON has not been studied.
- The efficacy of MEPRON in subjects who are failing therapy with TMP-SMX has also not been studied.

2 DOSAGE AND ADMINISTRATION

- Prevention of PCP: 1,500 mg (10 mL) once daily with food (2.1)
- Treatment of PCP: 750 mg (5 mL) twice daily with food for 21 days (2.2)
- Supplied in foil pouches and bottles:
○Foil Pouch: For a 5-mL dose, take entire contents by mouth either by dispensing into a spoon or cup or directly into the mouth. For a 10-mL dose, take entire contents of 2 pouches. (2.3)

○Bottle: Shake bottle gently before use. (2.3)

3 DOSAGE FORMS AND STRENGTHS

Oral suspension: 750 mg per 5 mL (3)

4 CONTRAINDICATIONS

Known serious allergic/hypersensitivity reaction (e.g., angioedema, bronchospasm, throat tightness, urticaria) to atovaquone or any of the components of MEPRON. (4)

5 WARNINGS AND PRECAUTIONS

- Failure to administer MEPRON oral suspension with food may result in lower plasma atovaquone concentrations and may limit response to therapy. Patients with gastrointestinal disorders may have limited absorption resulting in suboptimal atovaquone concentrations. (5.1)
- Hepatotoxicity: Elevated liver chemistry tests and cases of hepatitis and fatal liver failure have been reported. (5.2)

6 ADVERSE REACTIONS

- PCP Prevention: The most frequent adverse reactions (≥25% that required discontinuation) were diarrhea, rash, headache, nausea, and fever. (6.1)
- PCP Treatment: The most frequent adverse reactions (≥14% that required discontinuation) were rash (including maculopapular), nausea, diarrhea, headache, vomiting, and fever. (6.1)

To report SUSPECTED ADVERSE REACTIONS, contact GlaxoSmithKline at 1-888-825-5249 or FDA at 1-800-FDA-1088 or www.fda.gov/medwatch.

7 DRUG INTERACTIONS

- Concomitant administration of rifampin or rifabutin reduces atovaquone concentrations; concomitant use with MEPRON oral suspension is not recommended. (7.1)
- Concomitant administration of tetracycline reduces atovaquone concentrations; use caution when coadministering. Monitor patients for potential loss of efficacy of MEPRON if coadministration of tetracycline is necessary. (7.2)
- Concomitant administration with metoclopramide reduces atovaquone concentrations; administer concomitantly only if other antiemetics are not available. (7.3)
- Concomitant administration of indinavir reduces indinavir trough concentrations; use caution when coadministering. Monitor patients for potential loss of efficacy of indinavir if coadministration is necessary. (7.4)

8 USE IN SPECIFIC POPULATIONS

Lactation: Breastfeeding is not recommended in mothers with HIV-1 infection due to the potential for HIV-1 transmission. (8.2)

FULL PRESCRIBING INFORMATION

1 INDICATIONS AND USAGE

1.1 Prevention of Pneumocystis jirovecii Pneumonia

MEPRON oral suspension is indicated for the prevention of Pneumocystis jirovecii pneumonia (PCP) in adults and adolescents (aged 13 years and older) who cannot tolerate trimethoprim-sulfamethoxazole (TMP-SMX).

1.2 Treatment of Mild-to-Moderate Pneumocystis jirovecii Pneumonia

MEPRON oral suspension is indicated for the acute oral treatment of mild-to-moderate PCP in adults and adolescents (aged 13 years and older) who cannot tolerate TMP-SMX.

1.3 Limitations of Use

Clinical experience with MEPRON for the treatment of PCP has been limited to subjects with mild-to-moderate PCP (alveolar-arterial oxygen diffusion gradient [(A-a)DO2] ≤45 mm Hg). Treatment of more severe episodes of PCP with MEPRON has not been studied. The efficacy of MEPRON in subjects who are failing therapy with TMP-SMX has also not been studied.

2 DOSAGE AND ADMINISTRATION

2.1 Dosage for the Prevention of P. jirovecii Pneumonia

The recommended oral dosage is 1,500 mg (10 mL) once daily administered with food.

2.2 Dosage for the Treatment of Mild-to-Moderate P. jirovecii Pneumonia

The recommended oral dosage is 750 mg (5 mL) twice daily (total daily dose = 1,500 mg) administered with food for 21 days.

2.3 Important Administration Instructions

Administer MEPRON oral suspension with food to avoid low plasma atovaquone concentrations that may limit response to therapy [see Warnings and Precautions (5.1), Clinical Pharmacology (12.3)].

MEPRON Foil Pouch

- Open each 5-mL pouch by folding along the dotted line and tearing open at horizontal slit as directed by arrow on pouch.
- For a 5-mL dose, take entire contents either by placing directly into the mouth or by dispensing into a dosing spoon (5 mL) or cup prior to administration by mouth.
- For a 10-mL dose, take the entire contents of 2 pouches.

MEPRON Bottle

Shake bottle gently before administering the recommended dosage.

3 DOSAGE FORMS AND STRENGTHS

MEPRON is a bright yellow, citrus-flavored, oral suspension containing 750 mg of atovaquone per 5 mL. MEPRON is supplied in 210-mL bottles or 5-mL foil pouches.

4 CONTRAINDICATIONS

MEPRON oral suspension is contraindicated in patients who develop or have a history of hypersensitivity reactions (e.g., angioedema, bronchospasm, throat tightness, urticaria) to atovaquone or any of the components of MEPRON.

5 WARNINGS AND PRECAUTIONS

5.1 Risk of Limited Oral Absorption

Absorption of orally administered MEPRON oral suspension is limited but can be significantly increased when the drug is taken with food. Failure to administer MEPRON oral suspension with food may result in lower plasma atovaquone concentrations and may limit response to therapy. Consider therapy with other agents in patients who have difficulty taking MEPRON oral suspension with food or in patients who have gastrointestinal disorders that may limit absorption of oral medications [see Clinical Pharmacology (12.3)].

5.2 Hepatotoxicity

Cases of cholestatic hepatitis, elevated liver enzymes, and fatal liver failure have been reported in patients treated with atovaquone [see Adverse Reactions (6.2)].

If treating patients with severe hepatic impairment, closely monitor patients following administration of MEPRON.

6 ADVERSE REACTIONS

The following adverse reaction is discussed in another section of the labeling:

- Hepatotoxicity [see Warnings and Precautions (5.2)].

6.1 Clinical Trials Experience

Because clinical trials are conducted under widely varying conditions, adverse reaction rates observed in the clinical trials of a drug cannot be directly compared with rates in the clinical trials of another drug and may not reflect the rates observed in practice.

Additionally, because many subjects who participated in clinical trials with MEPRON had complications of advanced human immunodeficiency virus (HIV) disease, it was often difficult to distinguish adverse reactions caused by MEPRON from those caused by underlying medical conditions.

PCP Prevention Trials

In 2 clinical trials, MEPRON oral suspension was compared with dapsone or aerosolized pentamidine in HIV-1–infected adolescent (13 to 18 years) and adult subjects at risk of PCP (CD4 count <200 cells/mm^3 or a prior episode of PCP) and unable to tolerate TMP-SMX.

Dapsone Comparative Trial: In the dapsone comparative trial (n = 1,057), the majority of subjects were white (64%), male (88%), and receiving prophylaxis for PCP at randomization (73%); the mean age was 38 years. Subjects received MEPRON oral suspension 1,500 mg once daily (n = 536) or dapsone 100 mg once daily (n = 521); median durations of exposure were 6.7 and 6.5 months, respectively. Adverse reaction data were collected only for adverse reactions requiring discontinuation of treatment, which occurred at similar frequencies in subjects treated with MEPRON oral suspension or dapsone (Table 1). Among subjects taking neither dapsone nor atovaquone at enrollment (n = 487), adverse reactions requiring discontinuation of treatment occurred in 43% of subjects treated with dapsone and 20% of subjects treated with MEPRON oral suspension. Gastrointestinal adverse reactions (nausea, diarrhea, and vomiting) were more frequently reported in subjects treated with MEPRON oral suspension (Table 1).

Table 1. Percentage (>2%) of Subjects with Selected Adverse Reactions Requiring Discontinuation of Treatment in the Dapsone Comparative PCP Prevention Trial
Adverse Reaction | All Subjects
Adverse Reaction | MEPRON Oral Suspension; 1,500 mg/day; (n = 536); % | Dapsone; 100 mg/day; (n = 521); %
Rash | 6.3 | 8.8
Nausea | 4.1 | 0.6
Diarrhea | 3.2 | 0.2
Vomiting | 2.2 | 0.6

Aerosolized Pentamidine Comparative Trial: In the aerosolized pentamidine comparative trial (n = 549), the majority of subjects were white (79%), male (92%), and were primary prophylaxis patients at enrollment (58%); the mean age was 38 years. Subjects received MEPRON oral suspension once daily at a dose of 750 mg (n = 188) or 1,500 mg (n = 175) or received aerosolized pentamidine 300 mg every 4 weeks (n = 186); the median durations of exposure were 6.2, 6.0, and 7.8 months, respectively. Table 2 summarizes the clinical adverse reactions reported by ≥20% of the subjects receiving either the 1,500-mg dose of MEPRON oral suspension or aerosolized pentamidine.

Rash occurred more often in subjects treated with MEPRON oral suspension (46%) than in subjects treated with aerosolized pentamidine (28%). Treatment‑limiting adverse reactions occurred in 25% of subjects treated with MEPRON oral suspension 1,500 mg once daily and in 7% of subjects treated with aerosolized pentamidine. The most frequent adverse reactions requiring discontinuation of dosing in the group receiving MEPRON oral suspension 1,500 mg once daily were rash (6%), diarrhea (4%), and nausea (3%). The most frequent adverse reaction requiring discontinuation of dosing in the group receiving aerosolized pentamidine was bronchospasm (2%).

Table 2. Percentage (≥20%) of Subjects with Selected Adverse Reactions in the Aerosolized Pentamidine Comparative PCP Prevention Trial
Adverse Reaction | MEPRON Oral Suspension; 1,500 mg/day; (n = 175); % | Aerosolized Pentamidine; (n = 186); %
Diarrhea | 42 | 35
Rash | 39 | 28
Headache | 28 | 22
Nausea | 26 | 23
Fever | 25 | 18
Rhinitis | 24 | 17

Other reactions occurring in ≥10% of subjects receiving the recommended dose of MEPRON oral suspension (1,500 mg once daily) included vomiting, sweating, flu syndrome, sinusitis, pruritus, insomnia, depression, and myalgia.

PCP Treatment Trials

Safety information is presented from 2 clinical efficacy trials of the MEPRON tablet formulation: 1) a randomized, double‑blind trial comparing MEPRON tablets with TMP‑SMX in subjects with acquired immunodeficiency syndrome (AIDS) and mild‑to‑moderate PCP [(A-a)DO2] ≤45 mm Hg and PaO2 ≥60 mm Hg on room air; 2) a randomized, open-label trial comparing MEPRON tablets with intravenous (IV) pentamidine isethionate in subjects with mild‑to‑moderate PCP who could not tolerate trimethoprim or sulfa antimicrobials.

TMP‑SMX Comparative Trial: In the TMP‑SMX comparative trial (n = 408), the majority of subjects were white (66%) and male (95%); the mean age was 36 years. Subjects received MEPRON 750 mg (three 250‑mg tablets) 3 times daily for 21 days or TMP 320 mg plus SMX 1,600 mg 3 times daily for 21 days; median durations of exposure were 21 and 15 days, respectively.

Table 3 summarizes all clinical adverse reactions reported by ≥10% of the trial population regardless of attribution. Nine percent of subjects who received MEPRON and 24% of subjects who received TMP‑SMX discontinued therapy due to an adverse reaction. Among the subjects who discontinued, 4% of subjects receiving MEPRON and 8% of subjects in the TMP-SMX group discontinued therapy due to rash.

The incidence of adverse reactions with MEPRON oral suspension at the recommended dose (750 mg twice daily) was similar to that seen with the tablet formulation.

Table 3. Percentage (≥10%) of Subjects with Selected Adverse Reactions in the TMPSMX Comparative PCP Treatment Trial
Adverse Reaction | MEPRON Tablets; (n = 203); % | TMP‑SMX; (n = 205); %
Rash (including maculopapular) | 23 | 34
Nausea | 21 | 44
Diarrhea | 19 | 7
Headache | 16 | 22
Vomiting | 14 | 35
Fever | 14 | 25
Insomnia | 10 | 9

Two percent of subjects treated with MEPRON and 7% of subjects treated with TMP‑SMX had therapy prematurely discontinued due to elevations in ALT/AST.

Pentamidine Comparative Trial: In the pentamidine comparative trial (n = 174), the majority of subjects in the primary therapy trial population (n = 145) were white (72%) and male (97%); the mean age was 37 years. Subjects received MEPRON 750 mg (three 250‑mg tablets) 3 times daily for 21 days or a 3- to 4‑mg/kg single pentamidine isethionate IV infusion daily for 21 days; the median durations of exposure were 21 and 14 days, respectively.

Table 4 summarizes the clinical adverse reactions reported by ≥10% of the primary therapy trial population regardless of attribution. Fewer subjects who received MEPRON reported adverse reactions than subjects who received pentamidine (63% vs. 72%). However, only 7% of subjects discontinued treatment with MEPRON due to adverse reactions, while 41% of subjects who received pentamidine discontinued treatment for this reason. Of the 5 subjects who discontinued therapy with MEPRON, 3 reported rash (4%). Rash was not severe in any subject. The most frequently cited reasons for discontinuation of pentamidine therapy were hypoglycemia (11%) and vomiting (9%).

Table 4. Percentage (≥10%) of Subjects with Selected Adverse Reactions in the Pentamidine Comparative PCP Treatment Trial (Primary Therapy Group)
Adverse Reaction | MEPRON Tablets; (n = 73); % | Pentamidine; (n = 71); %
Fever | 40 | 25
Nausea | 22 | 37
Rash | 22 | 13
Diarrhea | 21 | 31
Insomnia | 19 | 14
Headache | 18 | 28
Vomiting | 14 | 17
Cough | 14 | 1
Sweat | 10 | 3
Monilia, oral | 10 | 3

Laboratory abnormality was reported as the reason for discontinuation of treatment in 2 of 73 subjects (3%) who received MEPRON, and in 14 of 71 subjects (20%) who received pentamidine. One subject (1%) receiving MEPRON had elevated creatinine and BUN levels and 1 subject (1%) had elevated amylase levels. In this trial, elevated levels of amylase occurred in subjects (8% versus 4%) receiving MEPRON tablets or pentamidine, respectively.

6.2 Postmarketing Experience

The following adverse reactions have been identified during post-approval use of MEPRON oral suspension. Because these reactions are reported voluntarily from a population of uncertain size, it is not always possible to reliably estimate their frequency or establish a causal relationship to drug exposure.

Blood and Lymphatic System Disorders

Methemoglobinemia, thrombocytopenia.

Immune System Disorders

Hypersensitivity reactions including angioedema, bronchospasm, throat tightness, and urticaria.

Eye Disorders

Vortex keratopathy.

Gastrointestinal Disorders

Pancreatitis.

Hepatobiliary Disorders

Hepatitis, fatal liver failure.

Skin and Subcutaneous Tissue Disorders

Erythema multiforme, Stevens-Johnson syndrome, and skin desquamation.

Renal and Urinary Disorders

Acute renal impairment.

7 DRUG INTERACTIONS

7.1 Rifampin/Rifabutin

Concomitant administration of rifampin or rifabutin and MEPRON oral suspension is known to reduce atovaquone concentrations [see Clinical Pharmacology (12.3)]. Concomitant administration of MEPRON oral suspension and rifampin or rifabutin is not recommended.

7.2 Tetracycline

Concomitant administration of tetracycline and MEPRON oral suspension has been associated with a reduction in plasma concentrations of atovaquone [see Clinical Pharmacology (12.3)]. Caution should be used when prescribing tetracycline concomitantly with MEPRON oral suspension. Monitor patients for potential loss of efficacy of MEPRON if coadministration is necessary.

7.3 Metoclopramide

Metoclopramide may reduce the bioavailability of atovaquone and should be used only if other antiemetics are not available [see Clinical Pharmacology (12.3)].

7.4 Indinavir

Concomitant administration of atovaquone and indinavir did not result in any change in the steady-state AUC and Cmax of indinavir but resulted in a decrease in the Ctrough of indinavir [see Clinical Pharmacology (12.3)]. Caution should be exercised when prescribing MEPRON oral suspension with indinavir due to the decrease in trough concentrations of indinavir. Monitor patients for potential loss of efficacy of indinavir if coadministration with MEPRON oral suspension is necessary.

8 USE IN SPECIFIC POPULATIONS

8.1 Pregnancy

Risk Summary

Available data from postmarketing experience with use of MEPRON in pregnant women are insufficient to identify a drug-associated risk for major birth defects, miscarriage, or adverse maternal or fetal outcomes. Pregnant women with HIV who are infected with PCP are at increased risk of adverse pregnancy outcomes (see Clinical Considerations). Atovaquone given orally by gavage to pregnant rats and rabbits during organogenesis did not cause fetal malformations at plasma concentrations up to 3 times and 0.5 times, respectively, the estimated human exposure based on steady-state plasma concentrations (see Data).

The estimated background risk of major birth defects and miscarriage for the indicated population is unknown. All pregnancies have a background risk of birth defect, loss, or other adverse outcomes. In the U.S. general population, the background risk of major birth defects and miscarriage in clinically recognized pregnancies is 2% to 4% and 15% to 20%, respectively.

Clinical Considerations

Disease-Associated Maternal and/or Embryo/Fetal Risk: Pregnant women with HIV who are infected with PCP are at increased risk of severe illness and maternal death associated with PCP compared with non-pregnant women.

Data

Animal Data: Atovaquone administered in oral doses of 250, 500, and 1,000 mg/kg/day to pregnant rats during organogenesis (Gestation Day [GD] 6 to GD15) did not cause maternal or embryo-fetal toxicity at doses up to 1,000 mg/kg/day corresponding to maternal plasma concentrations approximately 3 times the estimated human exposure during the treatment of PCP based on steady-state plasma concentrations. In pregnant rabbits, atovaquone administered in oral doses of 300, 600, and 1,200 mg/kg/day during organogenesis (GD6 to GD18) caused decreased fetal body length at a maternally toxic dose of 1,200 mg/kg/day corresponding to a plasma concentration that is approximately 0.5 times the estimated human exposure based on steady-state plasma concentrations. In a pre- and post-natal study in rats, atovaquone administered in oral doses of 250, 500, and 1,000 mg/kg/day from GD15 until Lactation Day (LD) 20 did not impair the growth or developmental effects in first generation offspring at doses up to 1,000 mg/kg/day corresponding to approximately 3 times the estimated human exposure based on steady-state plasma concentrations during the treatment of PCP. Atovaquone crossed the placenta and was present in fetal rat and rabbit tissue.

8.2 Lactation

Risk Summary

The Centers for Disease Control and Prevention recommend that HIV-1–infected mothers not breastfeed their infants to avoid risking postnatal transmission of HIV-1. There are no data on the presence of atovaquone in human milk, the effects on the breastfed child, or the effects on milk production. Atovaquone was detected in rat milk when lactating rats were administered oral atovaquone (see Data). When a drug is present in animal milk, it is likely the drug will be present in human milk. Because of the potential for HIV-1 transmission to HIV-negative infants, instruct mothers with HIV-1 not to breastfeed if they are taking MEPRON for the prevention or treatment of PCP.

Data

In a rat study with doses of 10 and 250 mg/kg given orally by gavage on postpartum Day 11, atovaquone concentrations in the milk were 30% of the concurrent atovaquone concentrations in the maternal plasma at both doses. The concentration of drug in animal milk does not necessarily predict the concentration of drug in human milk.

8.4 Pediatric Use

Evidence of safety and effectiveness in pediatric patients (aged 12 years and younger) has not been established. In a trial of MEPRON oral suspension administered once daily with food for 12 days to 27 HIV-1–infected, asymptomatic infants and children aged between 1 month and 13 years, the pharmacokinetics of atovaquone were age-dependent. The average steady-state plasma atovaquone concentrations in the 24 subjects with available concentration data are shown in Table 5.

Table 5. Average Steady-state Plasma Atovaquone Concentrations in Pediatric Subjects
Age | Dose of MEPRON Oral Suspension
Age | 10 mg/kg | 30 mg/kg | 45 mg/kg
Age | Average Css in mcg/mL (mean ± SD)
1-3 months | 5.9; (n = 1) | 27.8 ± 5.8; (n = 4) | _
>3-24 months | 5.7 ± 5.1; (n = 4) | 9.8 ± 3.2; (n = 4) | 15.4 ± 6.6; (n = 4)
>2-13 years | 16.8 ± 6.4; (n = 4) | 37.1 ± 10.9; (n = 3) | _
Css = Concentration at steady state.

8.5 Geriatric Use

Clinical trials of MEPRON did not include sufficient numbers of subjects aged 65 years and older to determine whether they respond differently from younger subjects.

10 OVERDOSAGE

Overdoses up to 31,500 mg of atovaquone have been reported. In one such patient who also took an unspecified dose of dapsone, methemoglobinemia occurred. Rash has also been reported after overdose. There is no known antidote for atovaquone, and it is currently unknown if atovaquone is dialyzable.

11 DESCRIPTION

MEPRON (atovaquone oral suspension) is a quinone antimicrobial drug. The chemical name of atovaquone is trans-2-[4-(4-chlorophenyl)cyclohexyl]-3-hydroxy-1,4-naphthalenedione. Atovaquone is a yellow crystalline solid that is practically insoluble in water. It has a molecular weight of 366.84 and the molecular formula C22H19ClO3. The compound has the following structural formula:

MEPRON oral suspension is a formulation of micro‑fine particles of atovaquone.

Each 5 mL of MEPRON oral suspension contains 750 mg of atovaquone and the inactive ingredients benzyl alcohol, flavor, poloxamer 188, purified water, saccharin sodium, and xanthan gum.

12 CLINICAL PHARMACOLOGY

12.1 Mechanism of Action

Atovaquone is a quinone antimicrobial drug [see Microbiology (12.4)].

12.2 Pharmacodynamics

Relationship between Plasma Atovaquone Concentrations and Clinical Outcome

In a comparative clinical trial, HIV/AIDS subjects received atovaquone tablets 750 mg 3 times daily or TMP‑SMX for treatment of mild‑to‑moderate PCP for 21 days [see Clinical Studies (14.2)]; the relationship between atovaquone plasma concentrations and successful treatment outcome from 113 of these subjects for whom both steady-state drug concentrations and outcome data were available is shown in Table 6.

Table 6. Relationship between Plasma Atovaquone Concentrations and Successful Treatment Outcome
Steady‑State Plasma Atovaquone Concentrations; (mcg/mL) | Successful Treatmenta; No. of Successes/No. in Group; (%)
0 to <5 | 0/6 (0%)
5 to <10 | 18/26 (69%)
10 to <15 | 30/38 (79%)
15 to <20 | 18/19 (95%)
≥20 | 24/24 (100%)
a Successful treatment outcome was defined as improvement in clinical and respiratory measures persisting at least 4 weeks after cessation of therapy. Improvement in clinical and respiratory measures was assessed using a composite of parameters that included oral body temperature, respiratory rate, and severity scores for cough, dyspnea, and chest pain/tightness.

Cardiac Effects

The effect of MEPRON oral suspension on the QT interval is unknown in humans.

12.3 Pharmacokinetics

Plasma atovaquone concentrations do not increase proportionally with dose following ascending repeat-dose administration of MEPRON oral suspension in healthy subjects. When MEPRON oral suspension was administered with food at dosage regimens of 500 mg once daily, 750 mg once daily, and 1,000 mg once daily, mean (±SD) steady-state plasma atovaquone concentrations were 11.7 ± 4.8, 12.5 ± 5.8, and 13.5 ± 5.1 mcg/mL, respectively. The corresponding mean (±SD) Cmax concentrations were 15.1 ± 6.1, 15.3 ± 7.6, and 16.8 ± 6.4 mcg/mL.

Absorption

Atovaquone is a highly lipophilic compound with low aqueous solubility. The mean (±SD) absolute bioavailability of atovaquone from a 750‑mg dose of MEPRON oral suspension administered under fed conditions in 9 HIV-1–infected (CD4 >100 cells/mm^3) volunteers was 47% ± 15%.

Effect of Food: Administering MEPRON oral suspension with food enhances atovaquone bioavailability. Sixteen healthy subjects received a single 750-mg dose of MEPRON oral suspension after an overnight fast and following a meal (23 g fat: 610 kCal). The mean (±SD) atovaquone AUC under fasting and fed conditions were 324 ± 115 and 801 ± 320 h●mcg/mL, respectively, representing a 2.6 ± 1.0-fold increase.

Distribution

Following IV administration of atovaquone, the mean (±SD) volume of distribution at steady state (Vdss) was 0.60 ± 0.17 L/kg (n = 9). Atovaquone is extensively bound to plasma proteins (99.9%) over the concentration range of 1 to 90 mcg/mL. In 3 HIV-1–infected children who received 750 mg atovaquone as the tablet formulation 4 times daily for 2 weeks, the cerebrospinal fluid concentrations of atovaquone were 0.04, 0.14, and 0.26 mcg/mL, representing less than 1% of the plasma concentration.

Elimination

The mean (±SD) half-life of atovaquone was 62.5 ± 35.3 hours after IV administration and ranged from 67.0 ± 33.4 to 77.6 ± 23.1 hours following administration of MEPRON oral suspension.

Metabolism: The metabolism of atovaquone is unknown.

Excretion: Following oral administration of ^14C-labelled atovaquone to healthy subjects, greater than 94% of the dose was recovered as unchanged atovaquone in the feces over 21 days.

Specific Populations

Patients with Hepatic or Renal Impairment: The pharmacokinetics of atovaquone have not been studied in patients with hepatic or renal impairment.

HIV-Infected Subjects: When MEPRON oral suspension was administered to 5 HIV-1–infected subjects at a dose of 750 mg twice daily, the mean (±SD) steady-state plasma atovaquone concentration was 21.0 ± 4.9 mcg/mL and mean (±SD) Cmax was 24.0 ± 5.7 mcg/mL. The mean (±SD) minimum plasma atovaquone concentration (Cmin) associated with the 750‑mg twice-daily regimen was 16.7 ± 4.6 mcg/mL.

In an open-label PCP trial in 18 HIV-1–infected subjects, administration of MEPRON oral suspension 750 mg twice daily with meals resulted in a mean (±SD) steady‑state plasma atovaquone concentration of 22.0 ± 10.1 mcg/mL.

The mean (±SD) plasma clearance of atovaquone following IV administration in 9 HIV-1–infected subjects was 10.4 ± 5.5 mL/min (0.15 ± 0.09 mL/min/kg).

Drug Interaction Studies

Rifampin/Rifabutin: In a trial with 13 HIV-1–infected volunteers, the oral administration of rifampin 600 mg every 24 hours with MEPRON oral suspension 750 mg every 12 hours resulted in a 52% ± 13% decrease in the mean (±SD) steady‑state plasma atovaquone concentration and a 37% ± 42% increase in the mean (±SD) steady‑state plasma rifampin concentration. The half‑life of atovaquone decreased from 82 ± 36 hours when administered without rifampin to 50 ± 16 hours with rifampin. In a trial of 24 healthy volunteers, the oral administration of rifabutin 300 mg once daily with MEPRON oral suspension 750 mg twice daily resulted in a 34% decrease in the mean steady‑state plasma atovaquone concentration and a 19% decrease in the mean steady‑state plasma rifabutin concentration.

Tetracycline: Concomitant treatment with tetracycline has been associated with a 40% reduction in plasma concentrations of atovaquone.

Metoclopramide: Concomitant treatment with metoclopramide has been associated with a 50% reduction in steady-state atovaquone plasma concentrations.

Indinavir: Concomitant administration of atovaquone (750 mg twice daily with food for 14 days) and indinavir (800 mg three times daily without food for 14 days) did not result in any change in the steady‑state AUC and Cmax of indinavir, but resulted in a decrease in the Ctrough of indinavir (23% decrease [90% CI: 8%, 35%]).

Trimethoprim/Sulfamethoxazole (TMP-SMX): Concomitant administration of MEPRON oral suspension 500 mg once daily (not the approved dosage) and TMP-SMX in 6 HIV-infected adult subjects did not result in significant changes in either atovaquone or TMP-SMX exposure.

Zidovudine: The administration of atovaquone tablets 750 mg every 12 hours with zidovudine 200 mg every 8 hours to 14 HIV-1–infected subjects resulted in a 24% ± 12% decrease in zidovudine apparent oral clearance, leading to a 35% ± 23% increase in plasma zidovudine AUC. The glucuronide metabolite:parent ratio decreased from a mean of 4.5 when zidovudine was administered alone to 3.1 when zidovudine was administered with atovaquone tablets. This effect is minor and would not be expected to produce clinically significant events. Zidovudine had no effect on atovaquone pharmacokinetics.

12.4 Microbiology

Mechanism of Action

Atovaquone is a hydroxy-1,4-naphthoquinone, an analog of ubiquinone, with antipneumocystis activity. The mechanism of action against Pneumocystis jirovecii has not been fully elucidated. In Plasmodium species, the site of action appears to be the cytochrome bc1 complex (Complex III). Several metabolic enzymes are linked to the mitochondrial electron transport chain via ubiquinone. Inhibition of electron transport by atovaquone results in indirect inhibition of these enzymes. The ultimate metabolic effects of such blockade may include inhibition of nucleic acid and adenosine triphosphate (ATP) synthesis.

Antimicrobial Activity

Atovaquone is active against P. jirovecii [see Clinical Studies (14)].

Resistance

Phenotypic resistance to atovaquone in vitro has not been demonstrated for P. jirovecii. However, in 2 subjects who developed PCP after prophylaxis with atovaquone, DNA sequence analysis identified mutations in the predicted amino acid sequence of P. jirovecii cytochrome b (a likely target site for atovaquone). The clinical significance of this is unknown.

13 NONCLINICAL TOXICOLOGY

13.1 Carcinogenesis, Mutagenesis, Impairment of Fertility

Carcinogenicity studies in rats were negative; 24‑month studies in mice (dosed with 50, 100, or 200 mg/kg/day) showed treatment‑related increases in incidence of hepatocellular adenoma and hepatocellular carcinoma at all doses tested, which correlated with 1.4 to 3.6 times the average steady-state plasma concentrations in humans during acute treatment of PCP. Atovaquone was negative with or without metabolic activation in the Ames Salmonella mutagenicity assay, the mouse lymphoma mutagenesis assay, and the cultured human lymphocyte cytogenetic assay. No evidence of genotoxicity was observed in the in vivo mouse micronucleus assay.

Impairment of Fertility

Atovaquone administered by oral gavage in doses of 100, 300, or 1,000 mg/kg/day to adult male rats from 73 days prior to mating until 20 days after mating and to adult female rats from 14 days prior to mating until LD20 did not impair male or female fertility or early embryonic development at doses up to 1,000 mg/kg/day corresponding to plasma exposures of approximately 3 times the estimated human exposure based on steady-state plasma concentrations.

14 CLINICAL STUDIES

14.1 Prevention of PCP

The indication for prevention of PCP is based on the results of 2 clinical trials comparing MEPRON oral suspension with dapsone or aerosolized pentamidine in HIV-1–infected adolescent (aged 13 to 18 years) and adult subjects at risk of PCP (CD4 count <200 cells/mm^3 or a prior episode of PCP) and unable to tolerate TMP‑SMX.

Dapsone Comparative Trial

This open-label trial enrolled 1,057 subjects, randomized to receive MEPRON oral suspension 1,500 mg once daily (n = 536) or dapsone 100 mg once daily (n = 521). The majority of subjects were white (64%), male (88%), and receiving prophylaxis for PCP at randomization (73%); the mean age was 38 years. Median follow-up was 24 months. Subjects randomized to the dapsone arm who were seropositive for Toxoplasma gondii and had a CD4 count <100 cells/mm^3 also received pyrimethamine and folinic acid. PCP event rates are shown in Table 7. Mortality rates were similar.

Aerosolized Pentamidine Comparative Trial

This open-label trial enrolled 549 subjects, randomized to receive MEPRON oral suspension 1,500 mg once daily (n = 175), MEPRON oral suspension 750 mg once daily (n = 188), or aerosolized pentamidine 300 mg once monthly (n = 186). The majority of subjects were white (79%), male (92%), and were primary prophylaxis patients at enrollment (58%); the mean age was 38 years. Median follow-up was 11.3 months. The results of the PCP event rates appear in Table 7. Mortality rates were similar among the groups.

Table 7. Confirmed or Presumed/Probable PCP Events (As-Treated Analysis)a
Assessment | Trial 1 |  | Trial 2
Assessment | MEPRON Oral Suspension; 1,500 mg/day; (n = 527) | Dapsone; 100 mg/day; (n = 510) | MEPRON Oral Suspension; 750 mg/day; (n = 188) | MEPRON Oral Suspension; 1,500 mg/day; (n = 172) | Aerosolized; Pentamidine; 300 mg/month; (n = 169)
% | 15 | 19 | 23 | 18 | 17
Relative Riskb; (CI)c | 0.77; (0.57, 1.04) |  | 1.47; (0.86, 2.50) | 1.14; (0.63, 2.06)
a Those events occurring during or within 30 days of stopping assigned treatment.
b Relative risk <1 favors MEPRON and values >1 favor comparator. Trial results did not show superiority of MEPRON to the comparator.
c The confidence level of the interval for the dapsone comparative trial was 95% and for the pentamidine comparative trial was 97.5%.

An analysis of all PCP events (intent-to-treat analysis) for both trials showed results similar to those shown in Table 7.

14.2 Treatment of PCP

The indication for treatment of mild‑to‑moderate PCP is based on the results of 2 efficacy trials: a randomized, double‑blind trial comparing MEPRON tablets with TMP‑SMX in subjects with HIV/AIDS and mild‑to‑moderate PCP (defined in the protocol as [(A‑a)DO2] ≤45 mm Hg and PaO2 ≥60 mm Hg on room air) and a randomized open-label trial comparing MEPRON tablets with IV pentamidine isethionate in subjects with mild‑to‑moderate PCP who could not tolerate trimethoprim or sulfa antimicrobials. Both trials were conducted with the tablet formulation using 750 mg 3 times daily. Results from these efficacy trials established a relationship between plasma atovaquone concentrations and successful outcome. Successful outcome was defined as improvement in clinical and respiratory measures persisting at least 4 weeks after cessation of therapy [see Clinical Pharmacology (12.2)].

TMP‑SMX Comparative Trial

This double‑blind, randomized trial compared the safety and efficacy of MEPRON tablets with that of TMP‑SMX for the treatment of subjects with HIV/AIDS and histologically confirmed PCP. Only subjects with mild‑to‑moderate PCP were eligible for enrollment.

A total of 408 subjects were enrolled into the trial. The majority of subjects were white (66%) and male (95%); the mean age was 36 years. Eighty‑six subjects without histologic confirmation of PCP were excluded from the efficacy analyses. Of the 322 subjects with histologically confirmed PCP, 160 were randomized to receive 750 mg MEPRON (three 250-mg tablets) 3 times daily for 21 days and 162 were randomized to receive 320 mg TMP plus 1,600 mg SMX 3 times daily for 21 days. Therapy success was defined as improvement in clinical and respiratory measures persisting at least 4 weeks after cessation of therapy. Improvement in clinical and respiratory measures was assessed using a composite of parameters that included oral body temperature, respiratory rate, severity scores for cough, dyspnea, and chest pain/tightness. Therapy failures included lack of response, treatment discontinuation due to an adverse experience, and unevaluable.

There was a significant difference (P = 0.03) in mortality rates between the treatment groups favoring TMP-SMX. Among the 322 subjects with confirmed PCP, 13 of 160 (8%) subjects treated with MEPRON and 4 of 162 (2.5%) subjects receiving TMP‑SMX died during the 21‑day treatment course or 8‑week follow‑up period. In the intent‑to‑treat analysis for all 408 randomized subjects, there were 16 (8%) deaths among subjects treated with MEPRON and 7 (3.4%) deaths among subjects treated with TMP‑SMX (P = 0.051). Of the 13 subjects with confirmed PCP and treated with MEPRON who died, 4 died of PCP and 5 died with a combination of bacterial infections and PCP; bacterial infections did not appear to be a factor in any of the 4 deaths among TMP‑SMX‑treated subjects.

A correlation between plasma atovaquone concentrations and death demonstrated that subjects with lower plasma concentrations were more likely to die. For those subjects for whom Day 4 plasma atovaquone concentration data are available, 5 (63%) of 8 subjects with concentrations <5 mcg/mL died during participation in the trial. However, only 1 (2.0%) of the 49 subjects with Day 4 plasma atovaquone concentrations ≥5 mcg/mL died.

Sixty-two percent of subjects on MEPRON and 64% of subjects on TMP‑SMX were classified as protocol-defined therapy successes (Table 8).

Table 8. Outcome of Treatment for PCPPositive Subjects Enrolled in the TMPSMX Comparative Trial
Outcome of Therapya | Number of Subjects (%)
Outcome of Therapya | MEPRON Tablets; (n = 160) |  | TMP-SMX; (n = 162)
Therapy success | 99 | 62% | 103 | 64%
Therapy failure due to:
-Lack of response | 28 | 17% | 10 | 6%
-Adverse reaction | 11 | 7% | 33 | 20%
-Unevaluable | 22 | 14% | 16 | 10%
Required alternate PCP therapy during trial | 55 | 34% | 55 | 34%
a As defined by the protocol and described in trial description above.

The failure rate due to lack of response was significantly higher for subjects receiving MEPRON, while the failure rate due to an adverse reaction was significantly higher for subjects receiving TMP‑SMX.

Pentamidine Comparative Trial

This unblinded, randomized trial was designed to compare the safety and efficacy of MEPRON with that of pentamidine for the treatment of histologically-confirmed mild or moderate PCP in subjects with HIV/AIDS. Approximately 80% of the subjects either had a history of intolerance to trimethoprim or sulfa antimicrobials (the primary therapy group) or were experiencing intolerance to TMP‑SMX with treatment of an episode of PCP at the time of enrollment in the trial (the salvage treatment group). A total of 174 subjects were enrolled into the trial. Subjects were randomized to receive MEPRON 750 mg (three 250‑mg tablets) 3 times daily for 21 days or pentamidine isethionate 3- to 4‑mg/kg single IV infusion daily for 21 days. The majority of subjects were white (72%) and male (97%); the mean age was approximately 37 years. Thirty-nine subjects without histologic confirmation of PCP were excluded from the efficacy analyses. Of the 135 subjects with histologically-confirmed PCP, 70 were randomized to receive MEPRON and 65 to pentamidine. One hundred and ten (110) of these were in the primary therapy group and 25 were in the salvage therapy group. One subject in the primary therapy group randomized to receive pentamidine did not receive trial medication.

There was no difference in mortality rates between the treatment groups. Among the 135 subjects with confirmed PCP, 10 of 70 (14%) subjects receiving MEPRON and 9 of 65 (14%) subjects receiving pentamidine died during the 21‑day treatment course or 8‑week follow‑up period. In the intent‑to‑treat analysis for all subjects, there were 11 (12.5%) deaths among those treated with MEPRON and 12 (14%) deaths among those treated with pentamidine. Among subjects for whom Day 4 plasma atovaquone concentrations were available, 3 of 5 (60%) subjects with concentrations <5 mcg/mL died during participation in the trial. However, only 2 of 21 (9%) subjects with Day 4 plasma concentrations ≥5 mcg/mL died. The therapeutic outcomes for the 134 subjects who received trial medication in this trial are presented in Table 9.

Table 9. Outcome of Treatment for PCPPositive Subjects (%) Enrolled in the Pentamidine Comparative Trial
Outcome of Therapy | Primary Treatment |  |  |  | Salvage Treatment
Outcome of Therapy | MEPRON; (n = 56) |  | Pentamidine; (n = 53) |  | MEPRON; (n = 14) |  | Pentamidine; (n = 11)
Therapy success | 32 | 57% | 21 | 40% | 13 | 93% | 7 | 64%
Therapy failure due to:
-Lack of response | 16 | 29% | 9 | 17% | 0 |  | 0
-Adverse reaction | 2 | 3.6% | 19 | 36% | 0 |  | 3 | 27%
-Unevaluable | 6 | 11% | 4 | 8% | 1 | 7% | 1 | 9%
Required alternate PCP therapy during trial | 19 | 34% | 29 | 55% | 0 |  | 4 | 36%

16 HOW SUPPLIED/STORAGE AND HANDLING

MEPRON oral suspension (bright yellow, citrus-flavored) containing 750 mg atovaquone per 5 mL.

- Bottle of 210 mL with child-resistant cap (NDC 0173-0665-18). Store at 15°C to 25°C (59°F to 77°F). Do not freeze. Dispense in tight container as defined in USP.
- 5-mL child‑resistant foil pouch ‑ unit dose pack of 42 (NDC 0173-0547-00). Store at 15°C to 25°C (59°F to 77°F). Do not freeze.

17 PATIENT COUNSELING INFORMATION

Administration Instructions

Instruct patients to:

- Ensure the prescribed dose of MEPRON oral suspension is taken as directed.
- Take their daily doses of MEPRON oral suspension with food, as food will significantly improve the absorption of the drug.
- Shake MEPRON oral suspension gently before use each time.

Lactation

Instruct mothers with HIV-1 infection not to breastfeed because HIV-1 can be passed to the baby in the breast milk [see Use in Specific Populations (8.2)].

Trademarks are owned by or licensed to the GSK group of companies.

Distributed by:

GlaxoSmithKline

Durham, NC 27701

©2023 GSK group of companies or its licensor.

MPR:11PI

PACKAGE LABEL

PRINCIPAL DISPLAY PANEL

NDC 0173-0665-18

MEPRON

(atovaquone oral suspension)

750 mg/5 mL

Each 5 mL (1 teaspoonful) contains 750 mg atovaquone.

Rx only

GSK

210 mL

See accompanying prescribing information for Dosage and Administration.

Store at 15o to 25oC (59o to 77oF).

DO NOT FREEZE. Dispense in a tight container as defined in USP.

SHAKE GENTLY BEFORE USING.

Distributed by:

GlaxoSmithKline

Durham, NC 27701

Made in India

A001306 (30000000001306) Rev. 2/24

PACKAGE LABEL

PRINCIPAL DISPLAY PANEL

NDC 0173-0547-00

MEPRON

(atovaquone oral suspension)

750 mg/ 5mL

Each 5 mL sachet (1 teaspoonful) contains 750 mg atovaquone.

Store at 15o to 25oC (59o to 77oF). DO NOT FREEZE.

Do not accept if security seal is missing or broken.

See accompanying prescribing information for Dosage and Administration.

5 mL

Rx only

Contains 42 sachets of 5 mL each

GSK

©2024 GSK group of companies or its licensor.

A001308 (30000000001308) Rev. 2/24